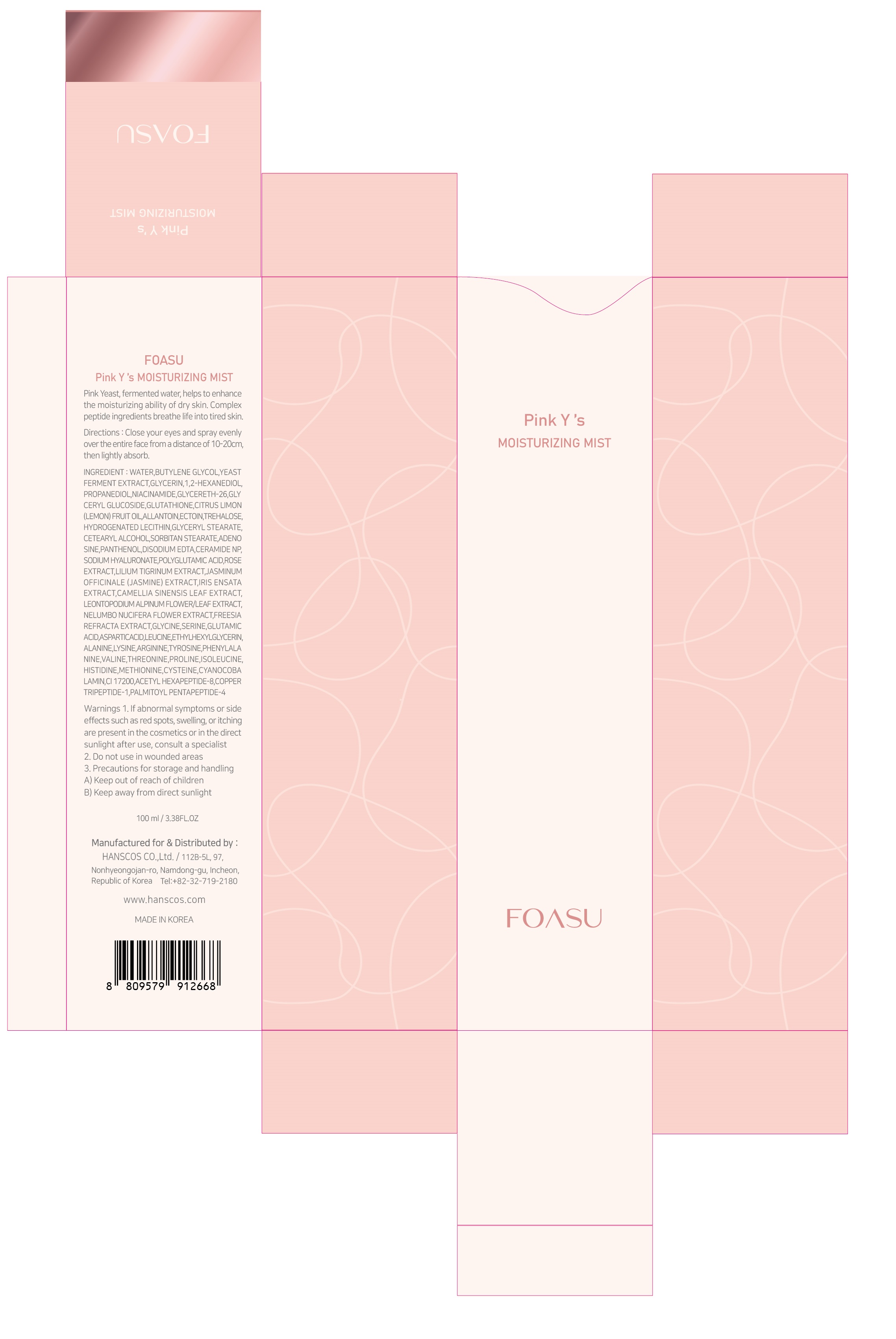 DRUG LABEL: FOASU Pink Y s MOISTURIZING MIST
NDC: 77964-002 | Form: LIQUID
Manufacturer: HANSCOS Co.,Ltd.
Category: otc | Type: HUMAN OTC DRUG LABEL
Date: 20220226

ACTIVE INGREDIENTS: ADENOSINE 0.04 g/100 mL; NIACINAMIDE 2 g/100 mL
INACTIVE INGREDIENTS: WATER; GLYCERIN

Active ingredient

niacinamide, adenosine

Purpose

skin protectant

Use

apply proper amount to the skin

Warnings

For external use only

1) Please consult your doctor if you experience side effects such as swelling, itching, or reddening on the area where you applied this product

2) Do not apply on wounds or cuts. 3) Do not store where children may reach, and avoid keeping it exposed to direct sunlight.

Directions

for external use only

Inactive ingredients

WATER
BUTYLENE GLYCOL
YEAST FERMENT EXTRACT
GLYCERIN
1,2-HEXANEDIOL
PROPANEDIOL
GLYCERETH-26
GLYCERYL GLUCOSIDE
GLUTATHIONE
CITRUS LIMON (LEMON) FRUIT OIL
ALLANTOIN
ECTOIN
TREHALOSE
HYDROGENATED LECITHIN
GLYCERYL STEARATE
CETEARYL ALCOHOL
SORBITAN STEARATE
PANTHENOL
DISODIUM EDTA
CERAMIDE NP
SODIUM HYALURONATE
POLYGLUTAMIC ACID
ROSE EXTRACT
LILIUM TIGRINUM EXTRACT
JASMINUM OFFICINALE (JASMINE) EXTRACT
IRIS ENSATA EXTRACT
CAMELLIA SINENSIS LEAF EXTRACT
LEONTOPODIUM ALPINUM FLOWER/LEAF EXTRACT
NELUMBO NUCIFERA FLOWER EXTRACT
FREESIA REFRACTA EXTRACT
GLYCINE
SERINE
GLUTAMIC ACID
ASPARTIC ACID
LEUCINE
ETHYLHEXYLGLYCERIN
ALANINE
LYSINE
ARGININE
TYROSINE
PHENYLALANINE
VALINE
THREONINE
PROLINE
ISOLEUCINE
HISTIDINE
METHIONINE
CYSTEINE
CYANOCOBALAMIN
CI 17200
ACETYL HEXAPEPTIDE-8
COPPER TRIPEPTIDE-1
PALMITOYL PENTAPEPTIDE-4

Keep out of reach of children. If swallowed, get medical help or contact a Poison Control Center right away.